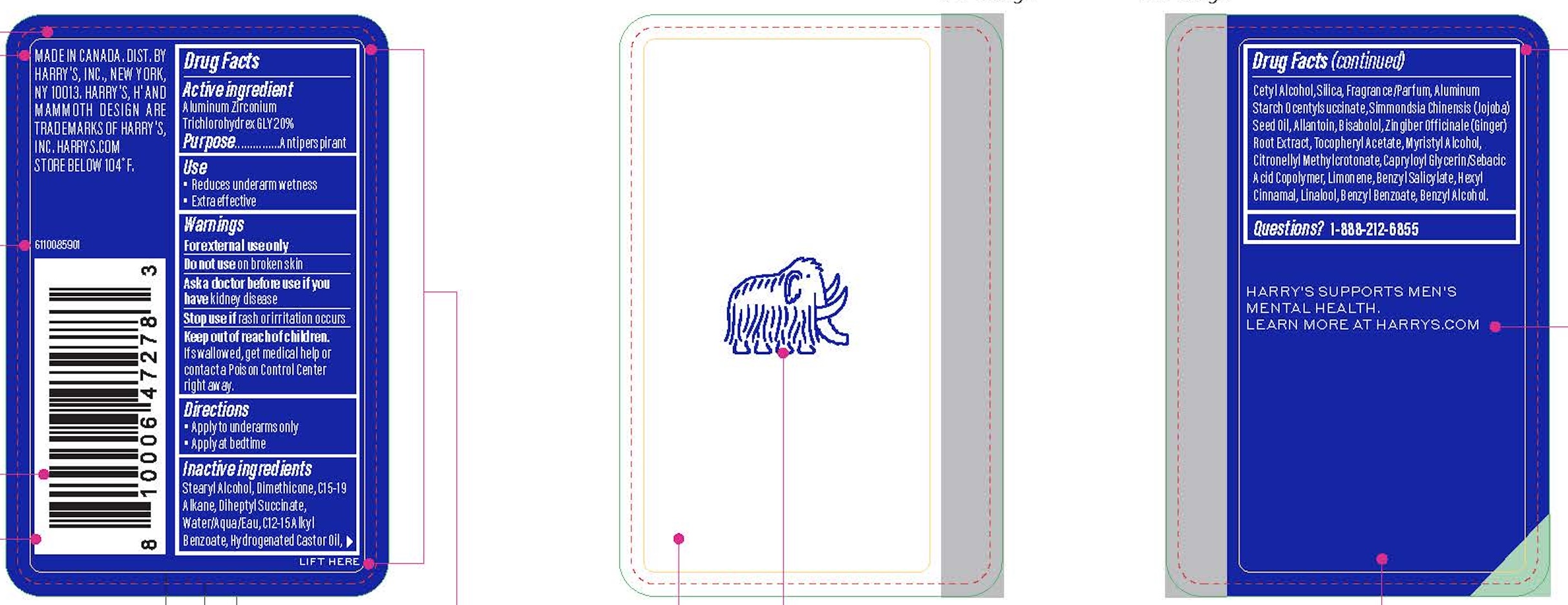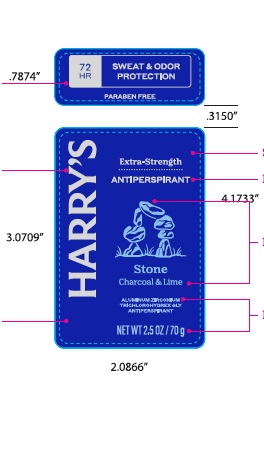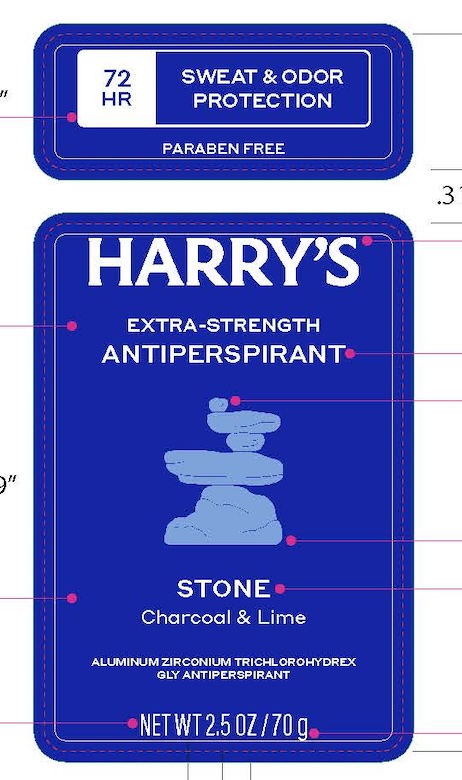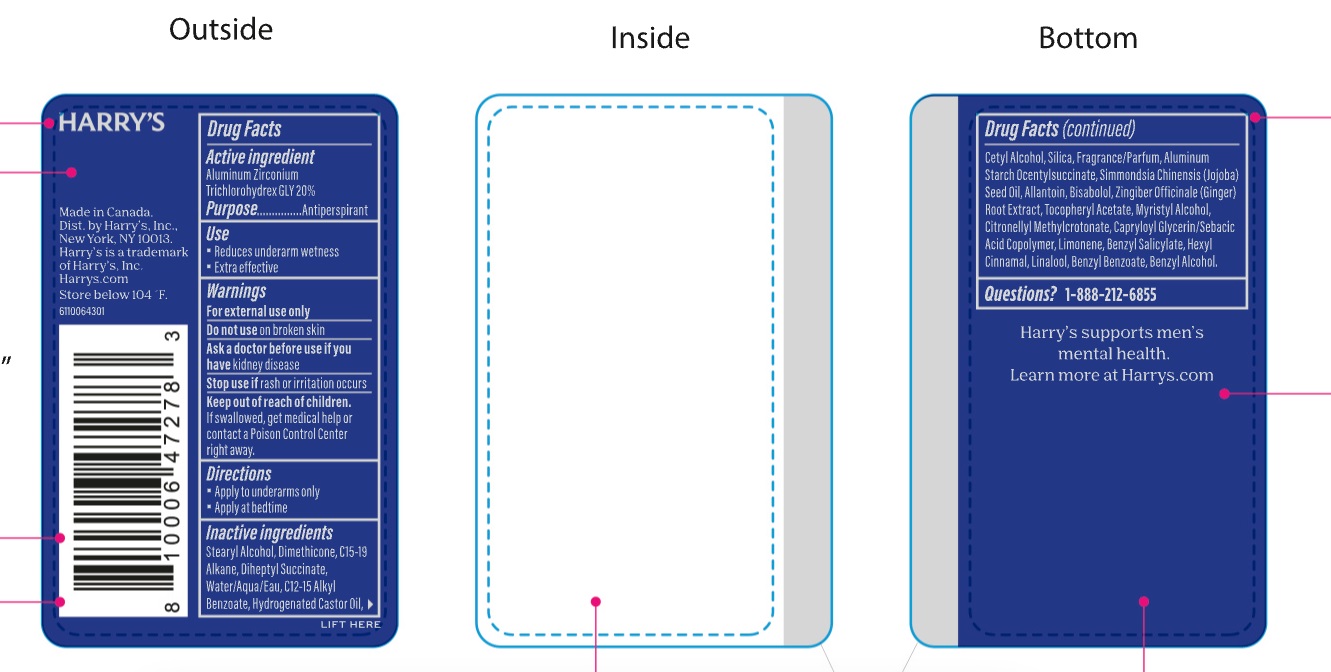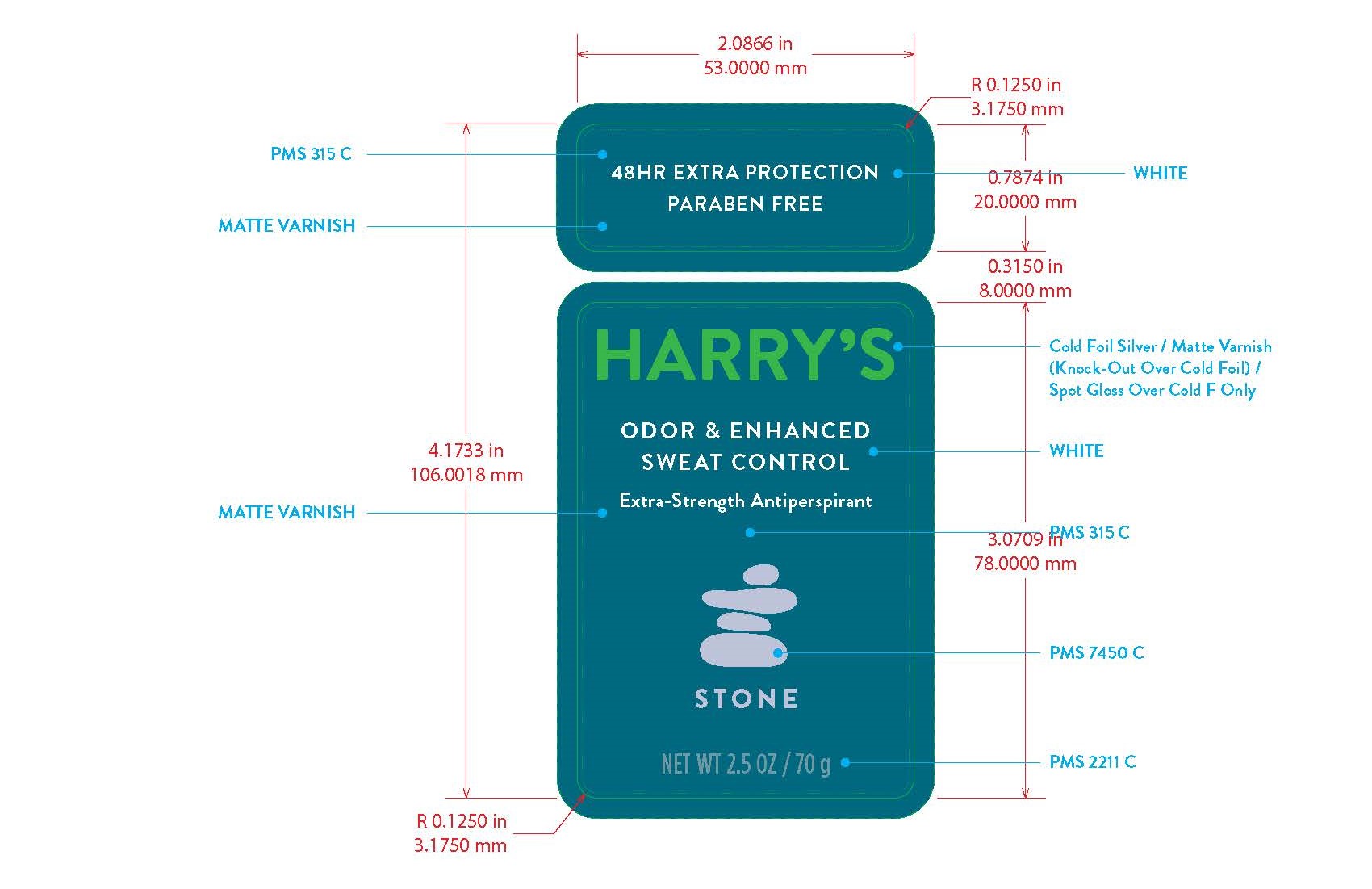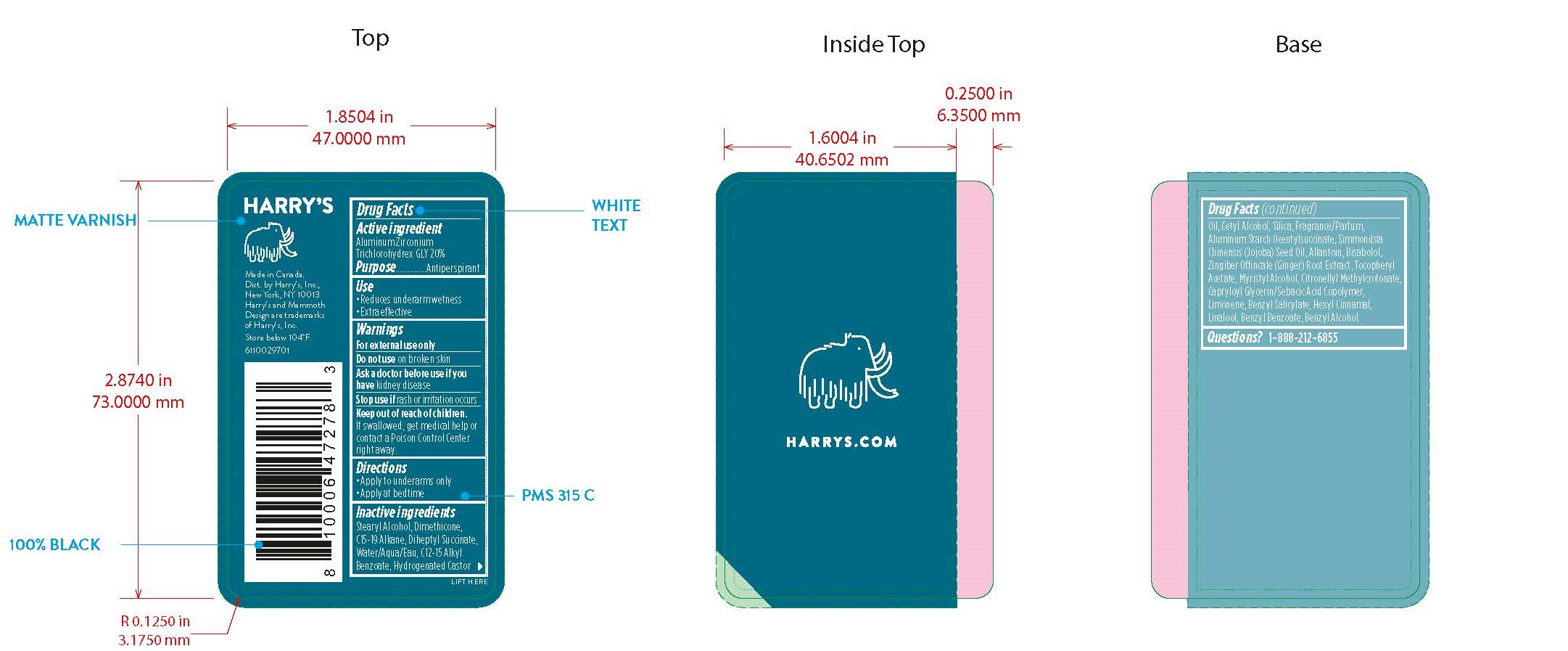 DRUG LABEL: Harrys Extra Strength Antiperspirant Stone
NDC: 70533-011 | Form: STICK
Manufacturer: Harry's Inc.
Category: otc | Type: HUMAN OTC DRUG LABEL
Date: 20251208

ACTIVE INGREDIENTS: ALUMINUM ZIRCONIUM TRICHLOROHYDREX GLY 200 mg/1 g
INACTIVE INGREDIENTS: STEARYL ALCOHOL; DIMETHICONE; HYDROGENATED CASTOR OIL; WATER; CETYL ALCOHOL; JOJOBA OIL; ALKYL (C12-15) BENZOATE; CAPRYLOYL GLYCERIN/SEBACIC ACID COPOLYMER (2000 MPA.S); .ALPHA.-BISABOLOL, (+/-)-; ALLANTOIN; BENZYL SALICYLATE; BENZYL ALCOHOL; LIMONENE, (+/-)-; FRAGRANCE 13576; C15-19 ALKANE; BENZYL BENZOATE; .ALPHA.-HEXYLCINNAMALDEHYDE; SILICON DIOXIDE; ALUMINUM STARCH OCTENYLSUCCINATE; .ALPHA.-TOCOPHEROL ACETATE; MYRISTYL ALCOHOL; CITRONELLYL METHYLCROTONATE; GINGER; LINALOOL, (+/-)-; DIHEPTYL SUCCINATE

Extra Strength AP - Stone

Active Ingredient

ALUMINUM ZIRCONIIUM TRICHLOROHYDREX GLY 20%

Purpose

Antiperspirant

Use

Reduces underarm wetness

Warnings

For external Use only

Do not use on broken skin

Ask doctor before use if you have kidney disease

Stop use if rash or irritation occurs.

Keep out of reach of children. If swallowed, get medical help or contact a Poison Control Center right away.

Directions

Apply to underarms only

Inactive Ingredients

STEARYL ALCOHOL, DIMETHICONE, C15-19 ALKANE, DIHEPTYL SUCCINATE, WATER/AQUA/EAU, C12-15 ALKYL BENZOATE, HYDROGENATED CASTOR OIL, CETYL ALCOHOL, SILICA, FRAGRANCE/PARFUM, ALUMINUM STARCH OCENTYLSUCCINATE, SIMMONDSIA CHINENSIS (JOJOBA) SEED OIL, ALLANTOIN, BISABOLOL, ZINGIBER OFFINCALE (GINGER) ROOT EXTRACT, TOCOPHERYL ACETATE, MYRISTYL ALCOHOL, CITRONELLYL METHYLCROTONATE, CAPRYLOYL GLYCERIN/SEBACIC ACID COPOLYMER, LIMONENE, BENZYL SALICYLATE, HEXYL CINNAMAL, LINALOOL, BENZYL BENZOATE, BENZYL ALCOHOL.

Questions?: 1-888-212-6855

PACKAGE LABEL

NDC: 70533-011-25